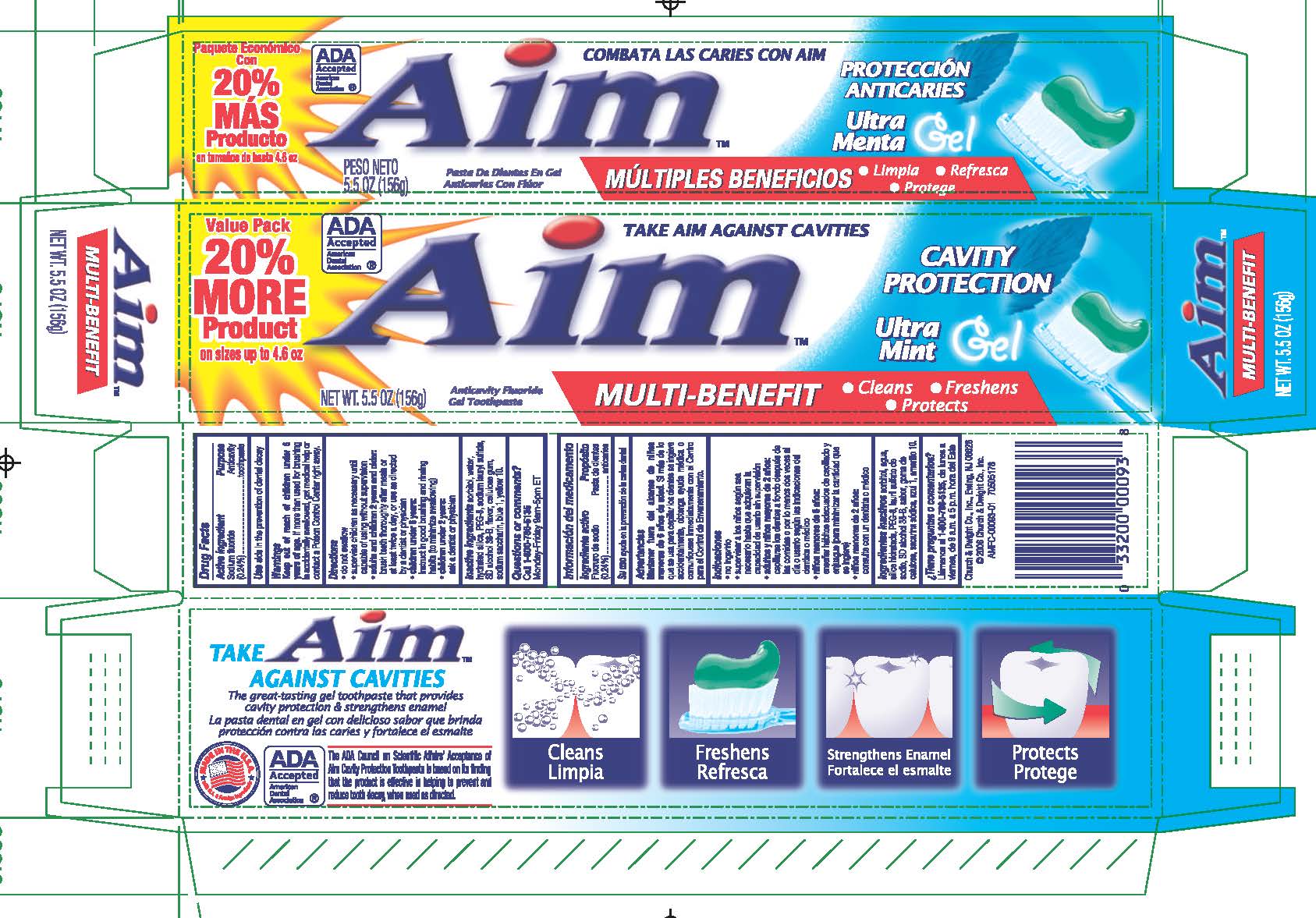 DRUG LABEL: AIM CAVITY PROTECTION
NDC: 10237-633 | Form: GEL, DENTIFRICE
Manufacturer: Church & Dwight Co., Inc.
Category: otc | Type: HUMAN OTC DRUG LABEL
Date: 20251203

ACTIVE INGREDIENTS: SODIUM FLUORIDE 2.4 mg/1 g
INACTIVE INGREDIENTS: WATER; HYDRATED SILICA; PEG-8 STEARATE; SODIUM LAURYL SULFATE; ALCOHOL; CARBOXYMETHYLCELLULOSE SODIUM; SACCHARIN SODIUM; FD&C BLUE NO. 1; D&C YELLOW NO. 10; SORBITOL

AIM CAVITY PROTECTION Multi Benefit

Active ingredients
Sodium fluoride (0.24%)

Purpose
Anticavity toothpaste

INDICATIONS AND USAGE

Use aids in the prevention of dental decay

Warnings
Keep out of reach of children under 6 years of age .

WARNINGS

If more than used for brushing is accidentally swallowed, get medical help or contact a Poison Control Center right away.

DOSAGE AND ADMINISTRATION

Directions do not swallow supervise children as necessary until capable of using without supervision

adults and children 2 years and older brush teeth thoroughly after meals or at least twice a day, or use as directed by a dentist or physician
children under 6 years instruct in good brushing and rinsing habits (to minimize swallowing)
children under 2 years ask a dentist or physician

INACTIVE INGREDIENT

Inactive ingredients sorbitol, water, hydrated silica, PEG-8, sodium lauryl sulfate, SD alcohol 38-B, flavor, cellulose gum, sodium saccharin, blue 1, yellow 10.

Questions or comments? Call 1-800-786-5135 Monday-Friday 9am-5pm ET

Principal Display Panel

Value Pack

20%

MORE

Product

on sizes up to 4.6 oz.

ADA

Accepted

American

Dental

Association

TAKE AIM AGAINST CAVITIES

Aim

CAVITY PROTECTION

Ultra Mint

Gel

MULTI-BENEFIT

Cleans

Freshens

Protects

Anticavity Fluoride Gel Toothpaste

NET WT. 5.5 OZ. (156g)